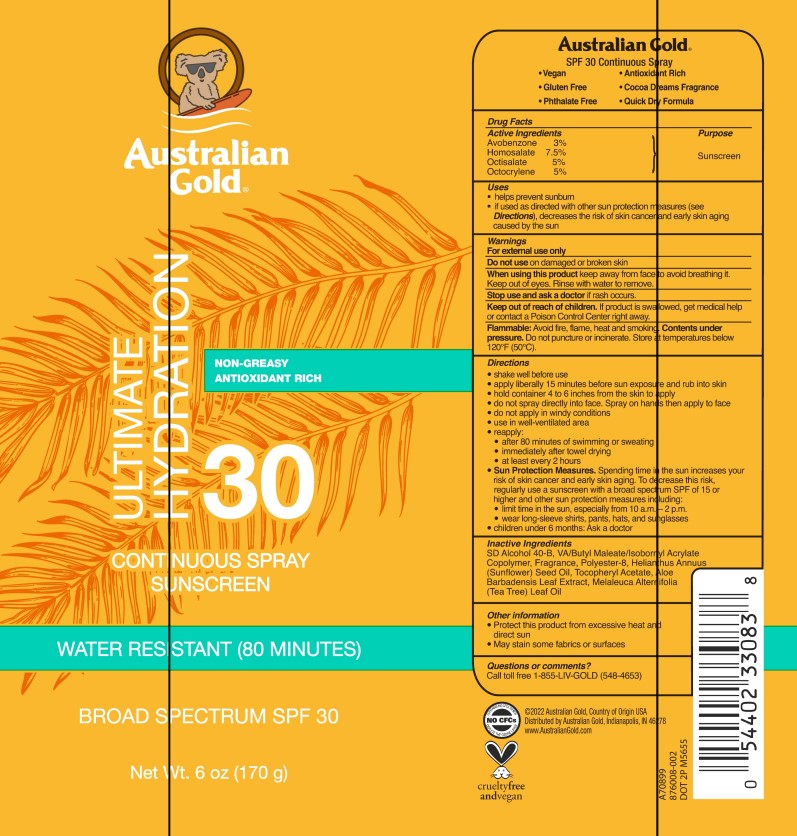 DRUG LABEL: Australian Gold
NDC: 13630-0260 | Form: SPRAY
Manufacturer: Prime Packaging, Inc.
Category: otc | Type: HUMAN OTC DRUG LABEL
Date: 20221114

ACTIVE INGREDIENTS: AVOBENZONE 25.17 g/1 mL; HOMOSALATE 62.93 g/1 mL; OCTISALATE 41.95 g/1 mL; OCTOCRYLENE 41.95 g/1 mL
INACTIVE INGREDIENTS: ALOE VERA LEAF; SUNFLOWER OIL; .ALPHA.-TOCOPHEROL ACETATE; ISOBORNYL ACRYLATE; ALCOHOL; POLYESTER-8 (1400 MW, CYANODIPHENYLPROPENOYL CAPPED); VINYL ACETATE; DIBUTYL MALEATE; TEA TREE OIL

AUSTRALIAN GOLD ULTIMATE HYDRATION 30 CONTINUOUS SPRAY SUNSCREEN

Active Ingredients

Avobenzone 3%

Homosalate 7.5%

Octisalate 5%

Octocrylene 5%

Purpose

Sunscreen

Uses

- helps prevent sunburn
- if used as directed with other sun protection measures (see Directions), decreases the risk of skin cancer and early skin aging caused by the sun

Warnings

For external use only

Do not use on damaged or broken skin

When using this product keep away from face to avoid breathing it. Keep out of eyes. Rinse with water to remove.

Stop use and ask a doctor if rash occurs.

Keep out of reach of children. If product is swalowed, get medical help or contact a Poison Control Center right away.

Flammable: Avoid fire, flame heat and smoking. Contents under pressure. Do not puncture or incinerate. Store at temperatures below 120°F (50°C).

Directions

- shake well before use
- apply liberally 15 minutes before sun exposure and rub into skin
- hold container 4 to 6 inches from the skin to apply
- do not spray directly onto face. Spray on hands then apply to face
- do not apply in windy conditions
- use in a well-ventilated area
- reapply:
- after 80 minutes of swimming or sweating
- immediately after towel drying
- at least every 2 hours
- Sun Protection Measures: Spending time in the sun increases your risk of skin cancer and early skin aging. To decrease this risk, regularly use a sunscreen with a broad spectrum SPF of 15 or higher and other sun protection measures including:
- limit time in the sun, especially from 10 a.m. – 2 p.m.
- wear long-sleeve shirts, pants, hats, and sunglasses
- children under 6 months: Ask a doctor

Inactive ingredients

SD Alcohol 40-B [Alohol Denat.], VA/Butyl Maleate/Isobornyl Acrylate Copolymer, Fragrance, Polyester-8, Helianthus Annuus (Sunflower) Seed Oil, Tocopheryl Acetate, Aloe Barbadensis Leaf Extract, Melaleuca Alternifolia (Tea Tree) Leaf Oil,

Other information

- Protect this product from excessive heat and direct sun
- May stain some fabrics or surfaces

Questions or comments?

Call toll free 1-885-LIV-GOLD (548-4653)